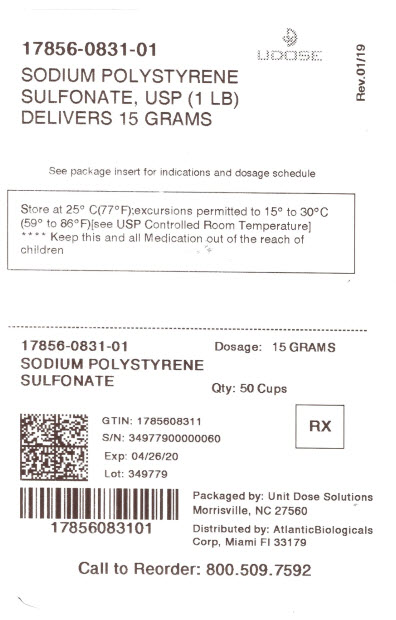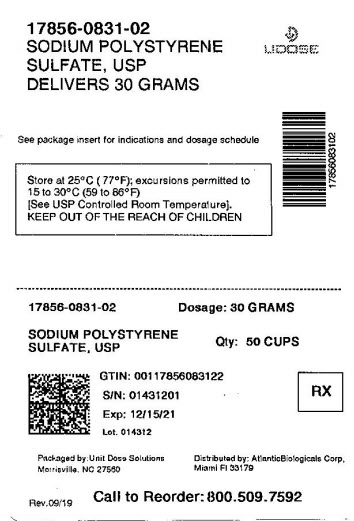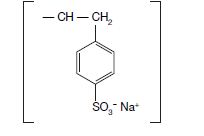 DRUG LABEL: Sodium Polystyrene Sulfonate
NDC: 17856-0831 | Form: POWDER, FOR SUSPENSION
Manufacturer: ATLANTIC BIOLOGICALS CORP.
Category: prescription | Type: HUMAN PRESCRIPTION DRUG LABEL
Date: 20250730

ACTIVE INGREDIENTS: SODIUM POLYSTYRENE SULFONATE 4.1 meq/1 g

Sodium Polystyrene Sulfonate Powder for Suspension
Cation - Exchange Resin
Rx only

DESCRIPTION

Sodium polystyrene sulfonate is a benzene, diethenyl-polymer, with ethenylbenzene, sulfonated, sodium salt and has the following structural formula

The drug is a cream to light brown finely ground, powdered form of sodium polystyrene sulfonate, a cation-exchange resin prepared in the sodium phase with an in vitroexchange capacity of approximately 3.1 mEq (in vivoapproximately 1 mEq) of potassium per gram. The sodium content is approximately 100 mg (4.1 mEq) per gram of the drug. It can be administered orally or in an enema.

CLINICAL PHARMACOLOGY

As the resin passes along the intestine or is retained in the colon after administration by enema, the sodium ions are partially released and are replaced by potassium ions. For the most part, this action occurs in the large intestine, which excretes potassium ions to a greater degree than does the small intestine. The efficiency of this process is limited and unpredictably variable. It commonly approximates the order of 33 percent but the range is so large that definitive indices of electrolyte balance must be clearly monitored.

Metabolic data are unavailable.

INDICATION AND USAGE

Sodium polystyrene sulfonate is indicated for the treatment of hyperkalemia.

CONTRAINDICATIONS

Sodium polystyrene sulfonate is contraindicated in the following conditions: patients with hypokalemia, patients with a history of hypersensitivity to polystyrene sulfonate resins, obstructive bowel disease, neonates with reduced gut motility (postoperatively or drug induced) and oral administration in neonates (see PRECAUTIONS).

WARNINGS

Intestinal Necrosis:

Cases of intestinal necrosis, which may be fatal, and other serious gastrointestinal adverse events (bleeding, ischemic colitis, perforation) have been reported in association with sodium polystyrene sulfonate use. The majority of these cases reported the concomitant use of sorbitol. Risk factors for gastrointestinal adverse events were present in many of the cases including prematurity, history of intestinal disease or surgery, hypovolemia, and renal insufficiency and failure. Concomitant administration of sorbitol is not recommended (see PRECAUTIONS, Drug Interactions).

- Use only in patients who have normal bowel function. Avoid use in patients who have not had a bowel movement post-surgery.
- Avoid use in patients who are at risk for developing constipation or impaction (including those with history of impaction, chronic constipation, inflammatory bowel disease, ischemic colitis, vascular intestinal atherosclerosis, previous bowel resection, or bowel obstruction).
- Discontinue use in patients who develop constipation.

Alternative Therapy in Severe Hyperkalemia:

Since effective lowering of serum potassium with sodium polystyrene sulfonate may take hours to days, treatment with this drug alone may be insufficient to rapidly correct severe hyperkalemia associated with states of rapid tissue breakdown (e.g., burns and renal failure) or hyperkalemia so marked as to constitute a medical emergency. Therefore, other definitive measures, including dialysis, should always be considered and may be imperative.

Hypokalemia:

Serious potassium deficiency can occur from therapy with sodium polystyrene sulfonate. The effect must be carefully controlled by frequent serum potassium determinations within each 24 hour period. Since intracellular potassium deficiency is not always reflected by serum potassium levels, the level at which treatment with sodium polystyrene sulfonate should be discontinued must be determined individually for each patient. Important aids in making this determination are the patient's clinical condition and electrocardiogram. Early clinical signs of severe hypokalemia include a pattern of irritable confusion and delayed thought processes.

Electrocardiographically, severe hypokalemia is often associated with a lengthened Q-T interval, widening, flattening, or inversion of the T wave, and prominent U waves. Also, cardiac arrhythmias may occur, such as premature atrial, nodal, and ventricular contractions, and supraventricular and ventricular tachycardias. The toxic effects of digitalis are likely to be exaggerated. Marked hypokalemia can also be manifested by severe muscle weakness, at times extending into frank paralysis.

Electrolyte Disturbances:

Like all cation-exchange resins, sodium polystyrene sulfonate is not totally selective (for potassium) in its actions, and small amounts of other cations such as magnesium and calcium can also be lost during treatment. Accordingly, patients receiving sodium polystyrene sulfonate should be monitored for all applicable electrolyte disturbances.

Systemic Alkalosis:

Systemic alkalosis has been reported after cation-exchange resins were administered orally in combination with nonabsorbable cation-donating antacids and laxatives such as magnesium hydroxide and aluminum carbonate. Magnesium hydroxide should not be administered with sodium polystyrene sulfonate. One case of grand mal seizure has been reported in a patient with chronic hypocalcemia of renal failure who was given sodium polystyrene sulfonate with magnesium hydroxide as laxative. (See PRECAUTIONS, Drug Interactions.)

PRECAUTIONS

Caution is advised when sodium polystyrene sulfonate is administered to patients who cannot tolerate even a small increase in sodium loads (i.e., severe congestive heart failure, severe hypertension, or marked edema). In such instances compensatory restriction of sodium intake from other sources may be indicated.

In the event of clinically significant constipation, treatment with sodium polystyrene sulfonate should be discontinued until normal bowel motion is resumed. (see WARNINGS, Intestinal Necrosis).

Drug Interactions

Antacids:

The simultaneous oral administration of sodium polystyrene sulfonate with nonabsorbable cation-donating antacids and laxatives may reduce the resin’s potassium exchange capability.

Non-absorbable cation-donating antacids and laxatives:

Systemic alkalosis has been reported after cation-exchange resins were administered orally in combination with nonabsorbable cation-donating antacids and laxatives such as magnesium hydroxide and aluminum carbonate. Magnesium hydroxide should not be administered with sodium polystyrene sulfonate. One case of grand mal seizure has been reported in a patient with chronic hypocalcemia of renal failure who was given sodium polystyrene sulfonate with magnesium hydroxide as a laxative.

Intestinal obstruction due to concretions of aluminum hydroxide when used in combination with sodium polystyrene sulfonate has been reported.

Digitalis:

The toxic effects of digitalis on the heart, especially various ventricular arrhythmias and A-V nodal dissociation, are likely to be exaggerated by hypokalemia, even in the face of serum digoxin concentrations in the "normal range". (See WARNINGS.)

Sorbitol:

Concomitant use of Sorbitol with sodium polystyrene sulfonate has been implicated in cases of intestinal necrosis, which may be fatal. Therefore, concomitant administration is not recommended. (See WARNINGS.)

Lithium:

Sodium polystyrene sulfonate may decrease absorption of lithium.

Thyroxine:

Sodium polystyrene sulfonate may decrease absorption of thyroxine.

Carcinogenesis, Mutagenesis, Impairment of Fertility

Studies have not been performed.

Pregnancy Category C

Animal reproduction studies have not been conducted with sodium polystyrene sulfonate. It is also not known whether sodium polystyrene sulfonate can cause fetal harm when administered to a pregnant woman or can affect reproduction capacity. Sodium polystyrene sulfonate should be given to a pregnant woman only if clearly needed.

Nursing Mothers

It is not known whether this drug is excreted in human milk. Because many drugs are excreted in human milk, caution should be exercised when sodium polystyrene sulfonate is administered to a nursing woman.

Pediatric Use

The effectiveness of sodium polystyrene sulfonate in pediatric patients has not been established. In neonates, sodium polystyrene sulfonate should not be given by the oral route. In both children and neonates particular care should be observed with rectal administration, as excessive dosage or inadequate dilution could result in impaction of the resin.

Due to the risk of digestive hemorrhage or intestinal necrosis, particular care should be observed in premature infants or low birth weight infants.

ADVERSE REACTIONS

Sodium polystyrene sulfonate may cause some degree of gastric irritation. Anorexia, nausea, vomiting, and constipation may occur especially if high doses are given. Also, hypokalemia, hypocalcemia, hypomagnesemia and significant sodium retention, and their related clinical manifestations, may occur (see WARNINGS). Occasionally diarrhea develops. Large doses in elderly individuals may cause fecal impaction (see PRECAUTIONS). Rare instances of intestinal necrosis have been reported. Intestinal obstruction due to concretions of aluminum hydroxide, when used in combination with sodium polystyrene sulfonate, has been reported.

The following events have been reported from worldwide post marketing experience:

- Fecal impaction following rectal administration, particularly in children;
- Gastrointestinal concretions (bezoars) following oral administration;
- Ischemic colitis, gastrointestinal tract ulceration or necrosis which could lead to intestinal perforation; and,
- Rare cases of acute bronchitis and/or broncho-pneumonia associated with inhalation of particles of polystyrene sulfonate.

OVERDOSAGE

Overdosage may result in electrolyte disturbances including hypokalemia, hypocalcemia, and hypomagnesemia. Biochemical disturbances resulting from over-dosage may give rise to clinical signs and symptoms of hypokalemia, including: irritability, confusion, delayed thought processes, muscle weakness, hyporeflexia, which may progress to frank paralysis and/or apnea. Tetany may occur. Electrocardiographic changes may be consistent with hypokalemia or hypercalcemia: cardiac arrhythmias may occur. Appropriate measures should be taken to correct serum electrolytes (potassium, calcium, magnesium), and the resin should be removed from the alimentary tract by appropriate use of laxatives or enemas.

DOSAGE AND ADMINISTRATION

Suspension of this drug should be freshly prepared and not stored beyond 24 hours.

The average daily adult dose of the resin is 15 g to 60 g. This is best provided by administering 15 g (approximately 4 levelteaspoons) of sodium polystyrene sulfonate one to four times daily. One gram of sodium polystyrene sulfonate contains 4.1 mEq of sodium; one level teaspoon contains approximately 3.5 g of sodium polystyrene sulfonate and 15 mEq of sodium. (A heaping teaspoon may contain as much as 10 g to 12 g of sodium polystyrene sulfonate.) Since the in vivoefficiency of sodium-potassium exchange resins is approximately 33 percent, about one third of the resin's actual sodium content is being delivered to the body.

In smaller children and infants, lower doses should be employed by using as a guide a rate of 1 mEq of potassium per gram of resin as the basis for calculation.

Each dose should be given as a suspension in a small quantity of water or, for greater palatability, in syrup. The amount of fluid usually ranges from 20 mL to 100 mL, depending on the dose, or may be simply determined by allowing 3 mL to 4 mL per gram of resin. Healthcare professionals should follow full aspiration precautions when administering this product, such as placing and maintaining the patient in an upright position while the resin is being administered.

The resin may be introduced into the stomach through a plastic tube and, if desired, mixed with a diet appropriate for a patient in renal failure.

The resin may also be given, although with less effective results, in an enema consisting (for adults) of 30 g to 50 g every six hours. Each dose is administered as a warm emulsion (at body temperature) in 100 mL of aqueous vehicle. The emulsion should be agitated gently during administration. The enema should be retained as long as possible and followed by a cleansing enema.

After an initial cleansing enema, a soft, large size (French 28) rubber tube is inserted into the rectum for a distance of about 20 cm, with the tip well into the sigmoid colon, and taped in place. The resin is then suspended in the appropriate amount of aqueous vehicle at body temperature and introduced by gravity, while the particles are kept in suspension by stirring. The suspension is flushed with 50 mL or 100 mL of fluid, following which the tube is clamped and left in place. If back leakage occurs, the hips are elevated on pillows or a knee-chest position is taken temporarily. A somewhat thicker suspension may be used, but care should be taken that no paste is formed, because the latter has a greatly reduced exchange surface and will be particularly ineffective if deposited in the rectal ampulla. The suspension is kept in the sigmoid colon for several hours, if possible. Then, the colon is irrigated with nonsodium containing solution at body temperature in order to remove the resin. Two quarts of flushing solution may be necessary. The returns are drained constantly through a Y tube connection. While the use of sorbitol is not recommended, particular attention should be paid to this cleansing enema if sorbitol has been used.

The intensity and duration of therapy depend upon the severity and resistance of hyperkalemia.

Sodium polystyrene sulfonate should not be heated for to do so may alter the exchange properties of the resin.

HOW SUPPLIED

Sodium polystyrene sulfonate is available as a cream to light brown, finely ground powder in jars of 1 pound (453.6 g), NDC51293-831-97

STORAGE AND HANDLING

Store at 25° C (77º F); excursions permitted to 15° - 30° C (59° - 86° F) [see USP Controlled Room Temperature]

DISTRIBUTED BY:

ATLANTIC BIOLOGICALS CORP.

20101 N.E 16TH PLACE

MIAMI, FL 33179

PRINCIPAL DISPLAY PANEL - 4.1mEq jar

NDC 17856-0831-1 Rx Only

Sodium Polystyrene
Sulfonate, USP

Average adult dose: 15 g (approximately 4 levelTeaspoons) one to four times
daily in water. See complete prescribing information.

The effect must be carefully controlled by frequent serum potassium determinations within
each 24 hour period. Sodium content approximately 60 mEq per 15 g.

Suspension should be freshly prepared and not stored beyond 24 hours.
Dispense in tight, light-resistant containers as defined in the official compendia.

Store at 25° C (77° F); excursions permitted to 15 to 30° C (59 to 86° F) [see USP Controlled Room Temperature]

15G (1 lb)

DISTRIBUTED BY: ATLANTIC BIOLOGICALS CORP. MIAMI, FL 33179